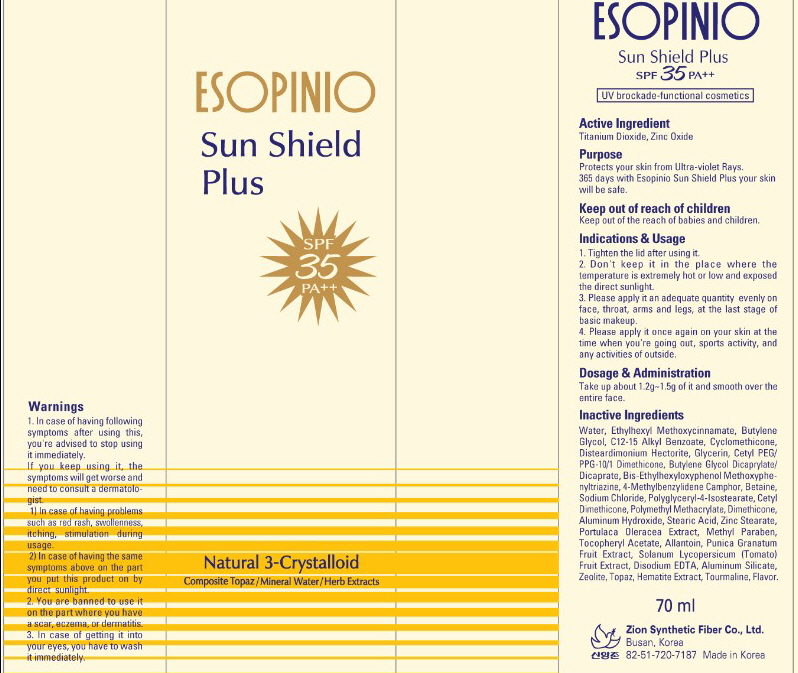 DRUG LABEL: ESOPINIO SUN SHIELD PLUS
NDC: 44781-110 | Form: CREAM
Manufacturer: ZION SYNTHETIC FIBER CO., LTD.
Category: otc | Type: HUMAN OTC DRUG LABEL
Date: 20110828

ACTIVE INGREDIENTS: TITANIUM DIOXIDE 2.55 mL/70 mL; Zinc Oxide 1.4 mL/70 mL
INACTIVE INGREDIENTS: Water; OCTINOXATE; Butylene Glycol; Cyclomethicone; Glycerin; Betaine; SODIUM CHLORIDE; Dimethicone; ALUMINUM HYDROXIDE; STEARIC ACID; ZINC STEARATE; METHYLPARABEN; ALLANTOIN; TOMATO; EDETATE DISODIUM; ALUMINUM SILICATE

Drug Facts

Active Ingredients: TITANIUM DIOXIDE, ZINC OXIDE

Inactive ingredients:

Water, Ethylhexyl Methoxycinnamate, Butylene Glycol, C12-15 Alkyl Benzoate, Cyclomethicone, Disteardimonium Hectorite, Glycerin, Cetyl PEG/PPG-10/1 Dimethicone,
Butylene Glycol Dicaprylate/Dicaprate, Bis-Ethylhexyloxyphenol Methoxyphenyltriazine, 4-Methylbenzylidene Camphor, Betaine, Sodium Chloride, Polyglyceryl-4-Isostearate,
Cetyl Dimethicone, Polymethyl Methacrylate, Dimethicone, Aluminum Hydroxide, Stearic Acid, Zinc Stearate, Portulaca Oleracea Extract, Methyl Paraben,
Tocopheryl Acetate, Allantoin, Punica Granatum Fruit Extract, Solanum Lycopersicum (Tomato) Fruit Extract, Disodium EDTA, Aluminum Silicate,
Zeolite, Topaz, Hematite Extract, Tourmaline, Flavor

Purpose:
Protects your skin from Ultra-violet Rays.
365 days with Esopinio Sun Shield Plus your skin will be safe.

Warnings:
In case of having following symptoms after using this, you're advised to stop using it immediately. If you keep using it, the symptoms will get worse and need to consult a dermatologist.
- In case of having problems such as red rash, swollenness, itching, stimulation during usage.
- In case of having the same symptoms above on the part you put this product on by direct sunlight.
You are banned to use it on the part where you have a scar, eczema, or dermatitis.
In case of getting it into your eyes, you have to wash it immediately.

Keep out of reach of children:

Keep out of reach of children.

Indications and Usage:
Tighten the lid after using it.
Don't keep it in the place where the temperature is extremely hot or low and exposed the direct sunlight.
Please apply it an adequate quantity evenly on face, throat, arms and legs at the last stage of basic makeup.
Please apply it once again on your skin at the time when you're going out, sports activity, and any activities of outside.

Dosage and Administration:
Take up about 1.2g - 1.5g of it and smooth over the entire face.